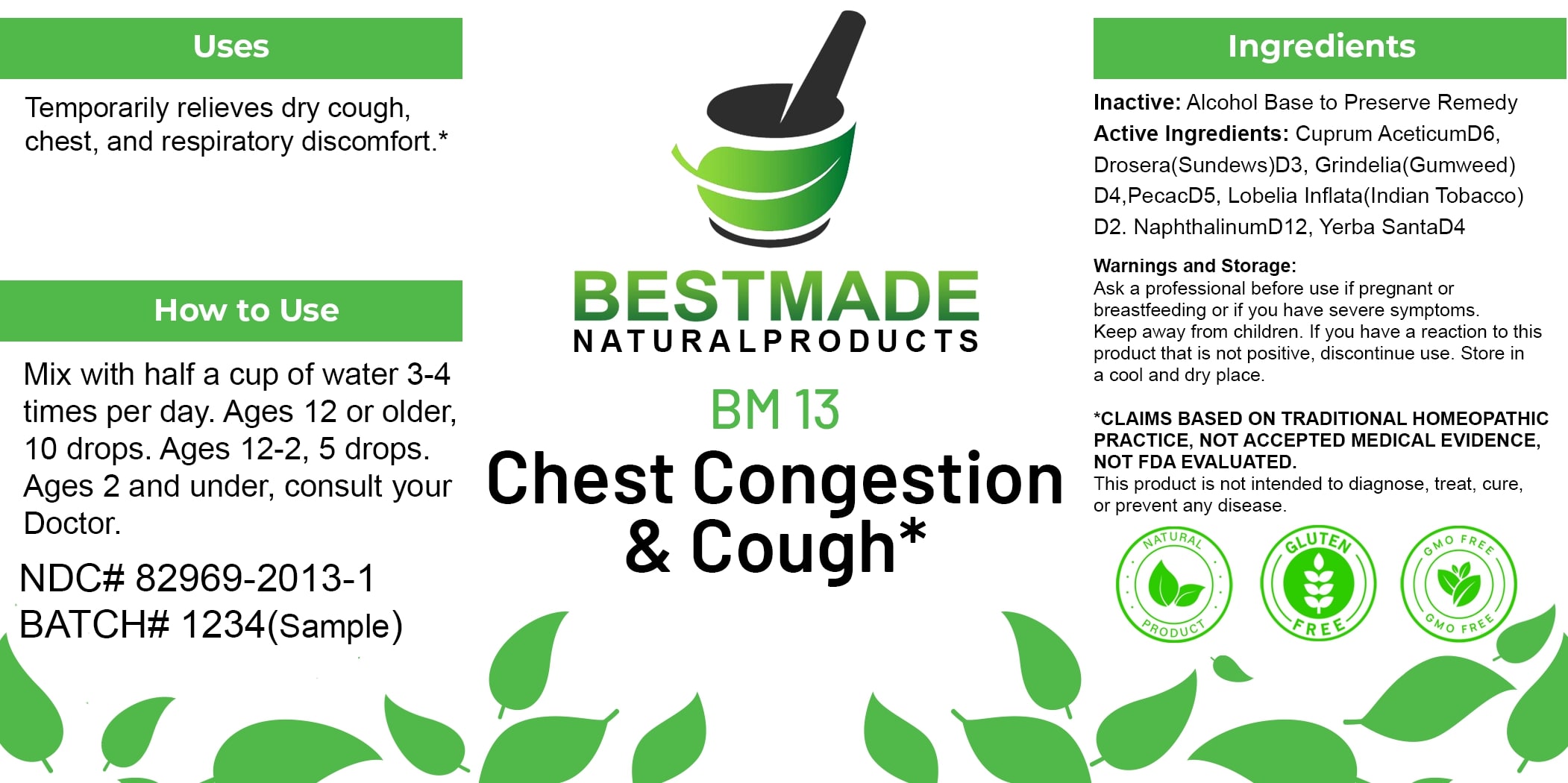 DRUG LABEL: Bestmade Natural Products BM13
NDC: 82969-2013 | Form: LIQUID
Manufacturer: Bestmade Natural Products
Category: homeopathic | Type: HUMAN OTC DRUG LABEL
Date: 20250122

ACTIVE INGREDIENTS: ATROPA BELLADONNA 30 [hp_C]/30 [hp_C]; DROSERA ROTUNDIFOLIA 30 [hp_C]/30 [hp_C]; NAPHTHALENE 30 [hp_C]/30 [hp_C]; ERIODICTYON CALIFORNICUM FLOWERING TOP 30 [hp_C]/30 [hp_C]; LOBELIA INFLATA 30 [hp_C]/30 [hp_C]; IPECAC 30 [hp_C]/30 [hp_C]; CUPRIC ACETATE 30 [hp_C]/30 [hp_C]; GRINDELIA HIRSUTULA FLOWERING TOP 30 [hp_C]/30 [hp_C]
INACTIVE INGREDIENTS: ALCOHOL 30 [hp_C]/30 [hp_C]

BM13

DOSAGE AND ADMINISTRATION

How to Use
Mix with half a cup of water 3-4 times per day. Ages 12 or older, 10 drops. Ages 12-2, 5 drops. Ages 2 and under, consult your Doctor.

INACTIVE INGREDIENT

Ingredients
Inactive: Alcohol Base to Preserve Remedy

Uses
Temporarily relieves dry cough, chest, and respiratory discomfort.*

*CLAIMS BASED ON TRADITIONAL HOMEOPATHIC PRACTICE, NOT ACCEPTED MEDICAL EVIDENCE, NOT FDA EVALUATED.
This product is not intended to diagnose, treat, cure, or prevent any disease.

Active Ingredients:

Cuprum Aceticum D6, Drosera (Sundews) D3, Grindelia (Gumweed) D4, Pecac D5, Lobelia Inflata (Indian Tobacco) D2, Naphthalinum D12, Yerba Santa D4

KEEP OUT OF REACH OF CHILDREN

Warnings and Storage:
Ask a professional before use if pregnant or breastfeeding or if you have severe symptoms. Keep away from children. If you have a reaction to this product that is not positive, discontinue use. Store in a cool and dry place.

Uses
Temporarily relieves dry cough, chest, and respiratory discomfort.*

*CLAIMS BASED ON TRADITIONAL HOMEOPATHIC PRACTICE, NOT ACCEPTED MEDICAL EVIDENCE, NOT FDA EVALUATED.
This product is not intended to diagnose, treat, cure, or prevent any disease.

Warnings and Storage:
Ask a professional before use if pregnant or breastfeeding or if you have severe symptoms. Keep away from children. If you have a reaction to this product that is not positive, discontinue use. Store in a cool and dry place.

*CLAIMS BASED ON TRADITIONAL HOMEOPATHIC PRACTICE, NOT ACCEPTED MEDICAL EVIDENCE, NOT FDA EVALUATED.
This product is not intended to diagnose, treat, cure, or prevent any disease.

Entire package label